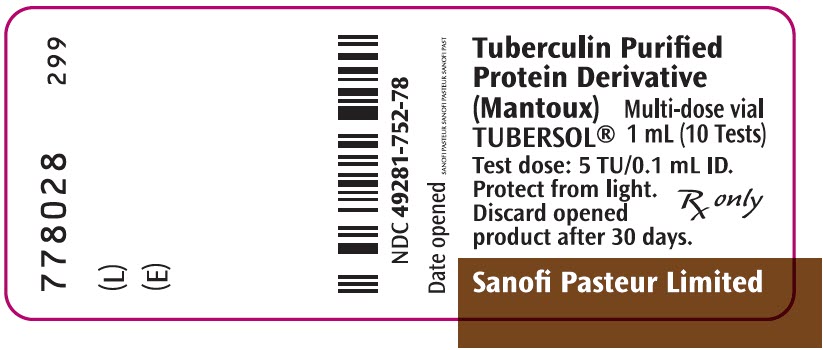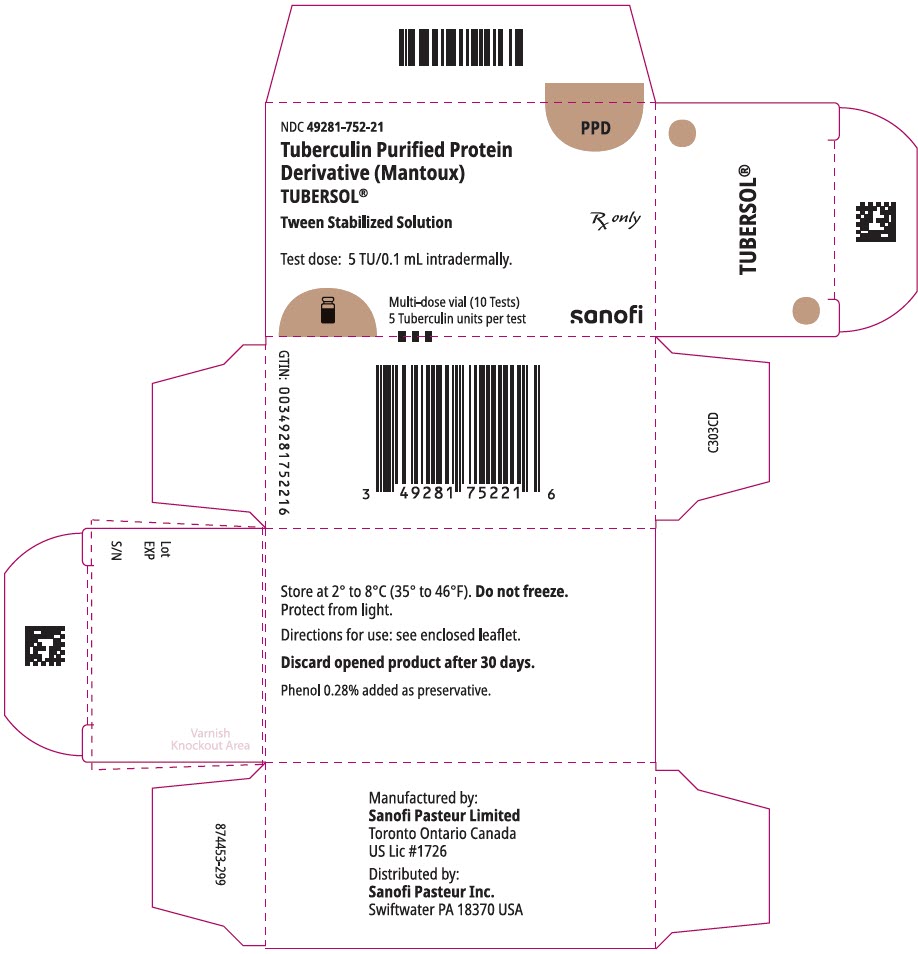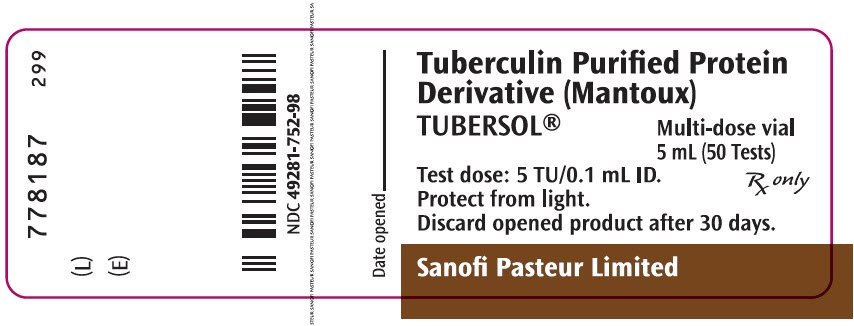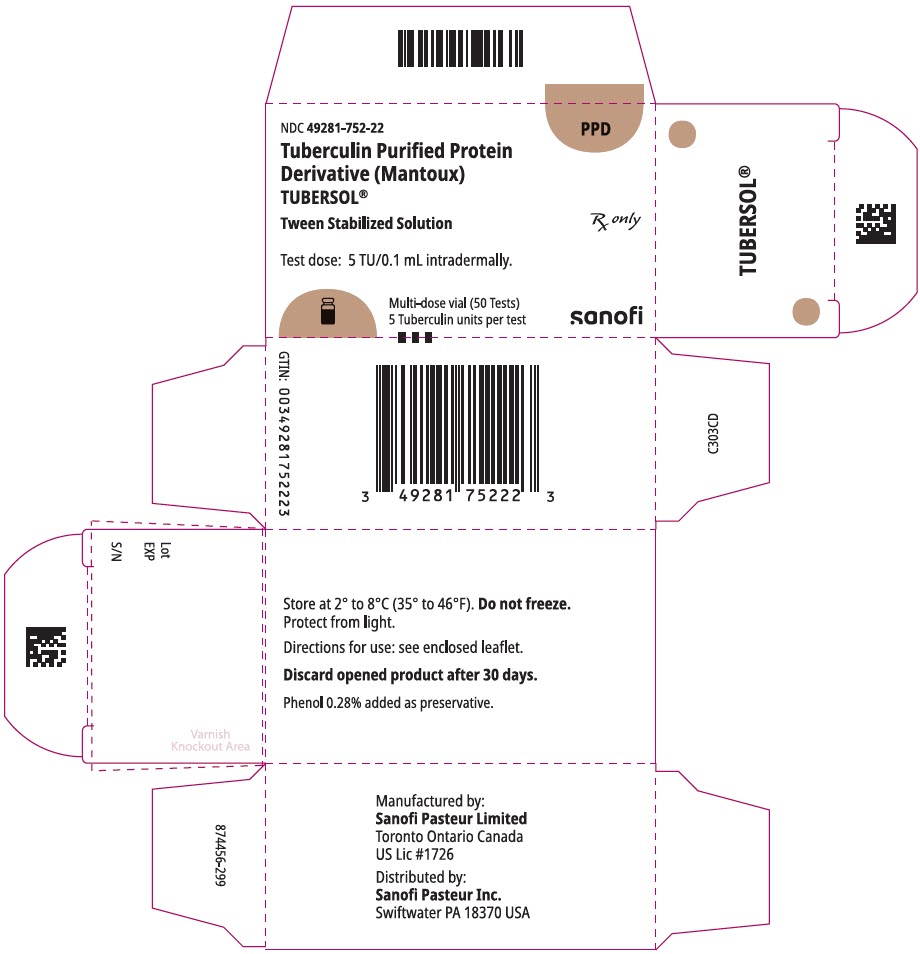 DRUG LABEL: TUBERSOL
NDC: 49281-752 | Form: INJECTION, SOLUTION
Manufacturer: Sanofi Pasteur Inc.
Category: prescription | Type: HUMAN PRESCRIPTION DRUG LABEL
Date: 20240125

ACTIVE INGREDIENTS: Tuberculin Purified Protein Derivative 5 [iU]/0.1 mL
INACTIVE INGREDIENTS: Polysorbate 80 0.0125 uL/0.1 mL; Phenol 0.35 mg/0.1 mL

Tuberculin Purified Protein Derivative
(Mantoux)
TUBERSOL®

AHFS Category: 36:84

Rx only

Diagnostic Antigen

(Aid in the detection of infection with Mycobacterium tuberculosis)

FOR INTRADERMAL USE

Polysorbate 80 Stabilized Solution of Tuberculin Purified Protein Derivative for Tuberculin Testing in Humans

DESCRIPTION

TUBERSOL® Tuberculin Purified Protein Derivative (Mantoux) (PPD) (1) for intradermal tuberculin testing is prepared from a large Master Batch Connaught Tuberculin (CT68) (2) and is a cell-free purified protein fraction obtained from a human strain of Mycobacterium tuberculosis grown on a protein-free synthetic medium and inactivated. (2) The use of a standard preparation derived from a single batch (CT68) has been adopted in order to eliminate batch to batch variation by the same manufacturer. (2)

TUBERSOL is a clear, colorless liquid.

TUBERSOL contains:
Purified protein derivative of M. tuberculosis | 5 TU per 0.1 mL
Polysorbate 80 | 0.0006%
Phenol | 0.22% to 0.35% w/v
in sterile isotonic phosphate buffered saline.

Before release, each successive lot is tested for potency in comparison with a reference standard.

Independent studies conducted by the US Public Health Service in humans have determined the amount of CT68 in stabilized solution necessary (3)(4)(5) to produce bio-equivalency with Tuberculin PPD-S (in phosphate buffer without polysorbate 80) using 5 US units (TU) Tuberculin PPD-S as the standard.

CLINICAL PHARMACOLOGY

Mechanism of Action

The sensitization following infection with mycobacteria occurs primarily in the regional lymph nodes. Small lymphocytes (T lymphocytes) proliferate in response to the antigenic stimulus to give rise to specifically sensitized lymphocytes. After 3-8 weeks, these lymphocytes enter the blood stream and circulate for years. (6) Subsequent restimulation of these sensitized lymphocytes with the same or a similar antigen, such as the intradermal injection of TUBERSOL, evokes a local reaction mediated by these cells. (7)

Characteristically, delayed hypersensitivity reactions to tuberculin begin at 5 to 6 hours, are maximal at 48 to 72 hours and subside over a period of days. The resultant immune response consists of induration due to cell infiltration and occasionally vesiculation and necrosis. Clinically, a delayed hypersensitivity reaction to tuberculin is a manifestation of previous infection with M tuberculosis or a variety of non-tuberculosis bacteria. In most cases sensitization is induced by natural mycobacterial infection or by vaccination with BCG Vaccine.

INDICATIONS AND USAGE

TUBERSOL Tuberculin Purified Protein Derivative (Mantoux), is indicated to aid diagnosis of tuberculosis infection (TB) in persons at increased risk of developing active disease.

The Centers for Disease Control and Prevention (CDC) have published guidelines regarding populations that would benefit from tuberculin skin testing (TST). Current recommendations can be accessed at: http://www.cdc.gov/tb/publications/factsheets/testing.htm.

Previous BCG vaccination is not a contraindication to tuberculin testing. The skin-test results of BCG vaccinated persons can be used to support or exclude the diagnosis of TB infection. However, an FDA-approved interferon gamma release assay is preferred over tuberculin skin test for persons 5 years of age and older who were previously vaccinated with BCG. (8)

CONTRAINDICATIONS

Allergy to any component of TUBERSOL or an anaphylactic or other allergic reaction to a previous test of tuberculin PPD is a contraindication to the use of TUBERSOL. (See DESCRIPTION and HOW SUPPLIED.)

TUBERSOL should not be administered to:

- Persons who have had a severe reaction (e.g., necrosis, blistering, anaphylactic shock, or ulcerations) to a previous TST,
- Persons with documented active tuberculosis or a clear history of treatment for TB infection or disease, (9)
- Persons with extensive burns or eczema.

WARNINGS

Hypersensitivity

Allergic reactions may occur following the use of TUBERSOL even in persons with no prior history of hypersensitivity to the product components. (10) Epinephrine injection (1:1,000) and other appropriate agents used for the control of immediate allergic reactions must be immediately available.

Syncope

Syncope (fainting) can occur in association with administration of injectable medicines, including TUBERSOL. Procedures should be in place to avoid falling injury and to restore cerebral perfusion following syncope.

PRECAUTIONS

General

Diagnostic Limitations

False positive or false negative tuberculin skin test reactions may occur in some individuals. (See Interpretation of the Test.)

False positive tuberculin reaction tests occur in individuals who have been infected with other mycobacteria, including vaccination with BCG.

Not all infected persons will have a delayed hypersensitivity reaction to a tuberculin test.

Many factors have been reported to cause a decreased ability to respond to the tuberculin test in the presence of tuberculous infection. (See Interpretation of the Test.)

Information for Patients

Prior to administration of TUBERSOL, the patient's current health status and medical history should be reviewed. The physician should review the patient's immunization history for possible sensitivity to components of TUBERSOL.

The healthcare provider should inform the patient of the need to return for the reading of the test. Self-reading of the test has been shown to be inaccurate and unreliable.

The healthcare provider should give the patient a permanent personal record. In addition, it is essential that the health professional record the testing history in the permanent medical record of each patient. This permanent office record should contain the name of the product, date given, dose, manufacturer, and lot number, as well as the test result in millimeters of induration (including 0 mm, if appropriate). Reporting results only as negative or positive is not satisfactory.

Drug Interactions

Reactivity to the test may be depressed or suppressed in persons who are receiving corticosteroids or immunosuppressive agents. (7)

Reactivity to TUBERSOL may be temporarily depressed by certain live virus vaccines (measles, mumps, rubella, oral polio, yellow fever, and varicella). If a parenteral live attenuated virus vaccine has been administered recently, tuberculin testing should be delayed for >1 month after vaccination. (7)(11) (See Interpretation of the Test.)

When tuberculin screening is required at the same time as a measles-containing vaccine or other parenteral live attenuated virus vaccine, simultaneous administration of TUBERSOL and the vaccine at separate sites is the preferred option.

CARCINOGENESIS, MUTAGENESIS, IMPAIRMENT OF FERTILITY

TUBERSOL has not been evaluated for its carcinogenic or mutagenic potentials or impairment of fertility.

Pregnancy

Animal reproduction studies have not been conducted with TUBERSOL. It is also not known whether TUBERSOL can cause fetal harm when administered to a pregnant woman or can affect reproduction capacity. TUBERSOL should be given to a pregnant woman only if clearly needed.

Nursing Mothers

It is not known whether TUBERSOL is excreted in human milk. Because many drugs are excreted in human milk, caution should be exercised when TUBERSOL is administered to a nursing woman.

Pediatric Use

There is no contraindication to tuberculin skin testing of infants. Infants <6 months of age who are infected with M. tuberculosis may not react to TUBERSOL. (See Interpretation of the Test.)

Geriatric Use

Clinical studies of TUBERSOL did not include sufficient numbers of subjects aged 65 and over to determine whether they respond differently from younger subjects.

ADVERSE REACTIONS

Induration at the TUBERSOL injection site is the expected reaction for a positive skin test. (See Interpretation of the Test.)

The information pertaining to adverse events has been compiled from historical clinical studies and post-marketing experience with TUBERSOL.

General disorders and administration site conditions

Injection site pain, injection site pruritus and injection site discomfort.
Injection site erythema or injection site rash (without induration) occurring within 12 hours of testing. These reactions do not indicate TB infection.
Injection site hemorrhage and injection site hematoma up to three days after the administration of the test.
Injection site vesicles, injection site ulcer or injection site necrosis in highly sensitive persons.
Injection site scar as a result of strongly positive reactions.
Pyrexia

Immune system disorders

Hypersensitivity, including anaphylaxis/anaphylactic reactions, angioedema, urticaria

Respiratory, thoracic, and mediastinal disorders

Stridor, dyspnea

Skin and subcutaneous tissue disorders

Rash, generalized rash

Nervous system disorders

Presyncope, syncope (including syncope associated with tonic-clonic movements and other seizure-like activity) sometimes resulting in transient loss of consciousness with injury

Reporting of Adverse Events

To report SUSPECTED ADVERSE REACTIONS, contact the Pharmacovigilance Department, Sanofi Pasteur Inc., Discovery Drive, Swiftwater, PA 18370 or call 1-800-822-2463 (1-800-VACCINE) or Food and Drug Administration (FDA) MEDWATCH Program at 1-800-332-1088 and www.fda.gov/medwatch.

DOSAGE AND ADMINISTRATION

Dosage

Five (5) tuberculin units (TU) per test dose of 0.1 mL is the standard strength used for intradermal (Mantoux) testing.

Method of Administration

TUBERSOL is indicated for intradermal injection only. Do not inject intravenously, intramuscularly, or subcutaneously. If subcutaneous injection occurs, the test cannot be interpreted.

Inspect for extraneous particulate matter and/or discoloration before use. If these conditions exist, do not administer the product.

Use a separate syringe and needle for each injection. (12)

The following procedure is recommended for performing the Mantoux test:

1. The preferred site of the test is the volar aspect of the forearm. Avoid areas on the skin that are red or swollen. Avoid visible veins.
2. Clean the skin site with a suitable germicide and allow the site to dry prior to injection of the antigen.
3. Administer the test dose (0.1 mL) of TUBERSOL with a 1 mL syringe calibrated in tenths and fitted with a short, one-quarter to one-half inch, 26 or 27 gauge needle.
4. Wipe the stopper of the vial with a suitable germicide and allow to dry before needle insertion. Then insert the needle gently through the stopper and draw 0.1 mL of TUBERSOL into the syringe. Avoid injection of excess air with removal of each dose so as not to over pressurize the vial and possibly cause seepage at the puncture site.
5. Insert the point of the needle into the most superficial layers of the skin with the needle bevel pointing upward and administer the dose by slow intradermal injection. If the intradermal injection is performed properly, a definite pale bleb will rise at the needle point, about 10 mm (^3/8") in diameter. This bleb will disperse within minutes. Do not dress the site.
6. A drop of blood may appear at the administration site following injection. Blot the site lightly to remove the blood but avoid squeezing out the injected tuberculin test fluid.

In the event of an improperly performed injection (i.e., no bleb formed), repeat the test immediately at another site, at least 2 inches from the first site and circle the second injection site as an indication that this is the site to be read.

Inform the patient of the need to return for the reading of the test by a trained health professional. Self-reading may be inaccurate and is strongly discouraged.

Interpretation of the Test

The skin test should be read by a trained health professional 48 to 72 hours after administration of TUBERSOL. Skin test sensitivity is indicated by induration only; redness should not be measured.

Measure the diameter of induration transversely to the long axis of the forearm and record the measurement in millimeters (including 0 mm). (7) The tip of a ballpoint pen, gently pushed at a 45° angle toward the site of injection, will stop at the edge of induration.

Also record presence and size (if present) of necrosis and edema, although these are not used in the interpretation of the test.

Positive Reactions

Tuberculin reactivity may indicate latent infection, prior infection and/or disease with M. tuberculosis and does not necessarily indicate the presence of active tuberculous disease. Persons showing positive tuberculin reactions should be considered positive by current public health guidelines and referred for further medical evaluation. (7)(9) The repeated testing of uninfected persons does not sensitize them to TUBERSOL. (6)(7)(9)

The significance of induration measurements in diagnosing latent TB infection must be considered in terms of the patient's history and the risk of developing active TB disease as indicated in Table 1. (9)

Table 1: Criteria for tuberculin positivity, by risk group
Reaction ≥5 mm of Induration | Reaction ≥10 mm of Induration | Reaction ≥15 mm of Induration
HIV-positive persons Recent contacts of tuberculosis (TB) case patients Fibrotic changes on chest radiograph consistent with prior TB Patients with organ transplants and other immunosuppressed patients (receiving the equivalent of ≥15 mg/d of prednisone for 1 month or more) [Risk of TB in patients treated with corticosteroids increases with higher dose and longer duration.] | Recent immigrants (i.e., within the last 5 yrs) from high prevalence countries Injection drug users Residents or employees [For persons who are otherwise at low risk and are tested at the start of employment, a reaction of ≥15 mm induration is considered positive.] of the following high-risk congregate settings: prisons and jails, nursing homes and other long-term facilities for the elderly, hospitals and other healthcare facilities, residential facilities for patients with acquired immunodeficiency syndrome (AIDS) and homeless shelters Mycobacteriology laboratory personnel Persons with the following clinical conditions that place them at high risk: silicosis, diabetes mellitus, chronic renal failure, some hematologic disorders (e.g., leukemias and lymphomas), other specific malignancies (e.g., carcinoma of the head or neck and lung), weight loss of ≥10% of ideal body weight, gastrectomy and jejunoileal bypass Children younger than 4 yrs of age or infants, children, and adolescents exposed to adults at high-risk | Persons with no risk factors for TB

A TST conversion is defined as an increase of ≥10 mm of induration within a 2-year period, regardless of age. (9)

The possibility should be considered that the skin test sensitivity may also be due to a previous contact with atypical mycobacteria or previous BCG vaccination. (7)(9)

Negative Reactions

An individual who does not show a positive reaction to 5 TU on the first test, but is suspected of being TB positive, may be retested with 5 TU. (See Booster Effect and Two-Step Testing.) Any individual who does not show a positive reaction to an initial injection of 5 TU, or a second test with 5 TU may be considered as tuberculin negative.

False Positive Reactions

False positive tuberculin reactions can occur in individuals who have been infected with other mycobacteria, including vaccination with BCG. (7) However, a diagnosis of M. tuberculosis infection and the use of preventive therapy should be considered for any BCG-vaccinated person who has a positive TST reaction, especially if the person has been, or is, at increased risk of acquiring TB infection. (See INDICATIONS AND USAGE.) (13)(14)

False Negative Reactions

Not all infected persons will have a delayed hypersensitivity reaction to a tuberculin test.

In those who are elderly or those who are being tested for the first time, reactions may develop slowly and may not peak until after 72 hours.

Since tuberculin sensitivity may take up to 8 weeks to develop following exposure to M. tuberculosis (see Mechanism of Action), persons who have a negative tuberculin test <8 weeks following possible TB exposure should be retested ≥8-10 weeks following the last known or suspected exposure. (15)

Altered Immune Status

Impaired or attenuated cell mediated immunity (CMI) can potentially cause a false negative tuberculin reaction. Many factors have been reported to cause a decreased ability to respond to the tuberculin test in the presence of tuberculous infection including viral infections (e.g., measles, mumps, chickenpox and HIV), live virus vaccinations (e.g., measles, mumps, rubella, oral polio and yellow fever), overwhelming tuberculosis, other bacterial infections, leukemia, sarcoidosis, fungal infections, metabolic derangements, low protein states, diseases affecting lymphoid organs, drugs (corticosteroids and many other immunosuppressive agents), and malignancy or stress. (7)(16)(17) A TST should be deferred for patients with major viral infections or live-virus vaccination in the past month. Persons with the common cold may be tuberculin tested.

Because TST results in HIV-infected individuals are less reliable as CD4 counts decline, screening should be completed as early as possible after HIV-infection occurs. (17)

Booster Effect and Two-Step Testing

If tuberculin testing will be conducted at regular intervals, for instance among healthcare workers or prison workers, two-step testing should be performed as a baseline to avoid interpreting a booster effect as a tuberculin conversion. If the first test showed either no reaction or a small reaction, the second test should be performed one to four weeks later. Both tests should be read and recorded at 48 to 72 hours. Patients with a second tuberculin test (booster) response of ≥10 mm should be considered to have experienced past TB infection. (13)(18)

Persons who do not boost when given repeat tests at one week, but whose tuberculin reactions change to positive after one year, should be considered to have newly acquired tuberculosis infection and managed accordingly. (6)

HOW SUPPLIED

TUBERSOL Tuberculin Purified Protein Derivative (Mantoux), bioequivalent to 5 US units (TU) PPD-S per test dose (0.1 mL) is supplied in:

1 mL multi-dose vial (10 tests). NDC No. 49281-752-78; package of 1 vial, NDC No. 49281-752-21

5 mL multi-dose vial (50 tests). NDC No. 49281-752-98; package of 1 vial, NDC No. 49281-752-22

The stopper of the vial for this product does not contain natural latex rubber.

STORAGE

Store at 2° to 8°C (35° to 46°F). (19) Do not freeze. Discard product if exposed to freezing.

Protect from light. Tuberculin PPD solutions can be adversely affected by exposure to light. The product should be stored in the dark except when doses are actually being withdrawn from the vial. (20)

A vial of TUBERSOL which has been entered and in use for 30 days should be discarded. (21)

Do not use after expiration date.

REFERENCES

1 Landi S. Preparation, purification, and stability of tuberculin. Appl Microbiol 1963;11:408-412.
2 Landi S, et al. Preparation and characterization of a large batch of tuberculin purified protein derivative (PPD-CT68). Ann Scalvo.1980;22:889-907.
3 Landi S, et al. Adsorption of tuberculin PPD to glass and plastic surfaces. Bull. WHO 1966;35:593-602.
4 Landi S, et al. Disparity of potency between stabilized and nonstabilized dilute tuberculin solutions. Am Rev Respir Dis 1971;104:385-393.
5 Landi S, et al. Stability of dilute solutions of tuberculin purified protein derivative. Tubercle 1978;59:121-133.
6 Menzies D. Interpretation of repeated tuberculin tests. Am J Respir Crit Care Med 1999;159:15-21.
7 American Thoracic Society: Diagnostic standards and classification of tuberculosis in adults and children. Am J Respir Crit Care Med 2000;161:1376-1395.
8 CDC. Updated Guidelines for Using Interferon Gamma Release Assays to Detect Mycobacterium tuberculosis Infection - United States, 2010. MMWR 2010; 59 (RR-5):1-25.
9 CDC. Targeted tuberculin testing and treatment of latent tuberculosis infection. MMWR 2000;49(RR-6):23-5.
10 Froeschle JE, et al. Immediate hypersensitivity reactions after use of tuberculin skin testing. Clin Infect Dis 2002;34:e12-13.
11 Brickman HF, et al. The timing of tuberculin tests in relation to immunization with live viral vaccines. Pediatrics: 1975;55:392-396.
12 CDC. General recommendations on immunization: recommendations of the Advisory Committee on Immunization Practices (ACIP) and the American Academy of Family Physicians (AAFP). MMWR 2002;51(RR-2):1-36.
13 CDC. Guidelines for preventing the transmission of Mycobacterium tuberculosis in health-care settings, 2005. MMWR 2005;54(RR-17):1-141.
14 CDC. The role of BCG vaccine in the prevention and control of tuberculosis in the United States. A joint statement by the Advisory Council for the Elimination of Tuberculosis and the Advisory Committee on Immunization Practices. MMWR 1996; 45(RR-4):1-18.
15 CDC. Guidelines for the Investigation of Contacts of Persons with Infectious Tuberculosis: Recommendations from the National Tuberculosis Controllers Association and CDC. MMWR 2005;54(RR-15):1-37.
16 Mori and Shiozawa. Suppression of tuberculin hypersensitivity caused by rubella infection. Am Rev Respir Dis 1985;886-888.
17 CDC. Guidelines for prevention and treatment of opportunistic infections in HIV-infected adults and adolescents. Recommendations from the CDC, the National Institutes of Health, and the HIV Medicine Association of Infectious Diseases Society of America. MMWR 2009;58(RR-4):1-207.
18 CDC. Prevention and control of tuberculosis in correctional and detention facilities: Recommendations from the CDC. MMWR 2006;55(RR-9):1-44.
19 Landi S, et al. Stability of dilute solution of tuberculin purified protein derivative at extreme temperatures. J Biol Stand 1981;9:195-199.
20 Landi S, et al. Effect of light on tuberculin purified protein derivative solutions. Am Rev Respir Dis 1975;111:52-61.
21 Landi S, et al. Effect of oxidation on the stability of tuberculin purified protein derivative (PPD) In: International Symposium on Tuberculins and BCG Vaccine. Basel: International Association of Biological Standardization, 1983. Dev Biol Stand 1986;58:545-552.

Manufactured by:
Sanofi Pasteur Limited
Toronto Ontario Canada

Distributed by:
Sanofi Pasteur Inc.
Swiftwater PA 18370 USA

Product Information as of
October 2021

TUBERSOL is a registered trademark of Sanofi Pasteur. ©, 2021 TUBERSOL®, Sanofi Pasteur Limited - All rights reserved

PRINCIPAL DISPLAY PANEL - 1 mL Vial Label

Tuberculin Purified
Protein Derivative
(Mantoux)
TUBERSOL®

Multi-dose vial
1 mL (10 Tests)

Test dose: 5 TU/0.1 mL ID.

Protect from light.

Discard opened
product after 30 days.

Rx only

Sanofi Pasteur Limited

PRINCIPAL DISPLAY PANEL - 1 mL Vial Carton

NDC 49281-752-21
PPD

Tuberculin Purified Protein
Derivative (Mantoux)
TUBERSOL®

Tween Stabilized Solution

Test dose: 5 TU/0.1 mL intradermally.

Multi-dose vial (10 Tests)
5 Tuberculin units per test

Rx only

sanofi

PRINCIPAL DISPLAY PANEL - 5 mL Vial Label

Tuberculin Purified Protein
Derivative (Mantoux)
TUBERSOL®

Multi-dose vial
5 mL (50 Tests)

Test dose: 5 TU/0.1 mL ID.

Protect from light.

Discard opened product after 30 days.

Rx only

Sanofi Pasteur Limited

PRINCIPAL DISPLAY PANEL - 5 mL Vial Carton

NDC 49281-752-22
PPD

Tuberculin Purified Protein
Derivative (Mantoux)
TUBERSOL®

Tween Stabilized Solution

Rx only

Test dose: 5 TU/0.1 mL intradermally.

Multi-dose vial (50 Tests)
5 Tuberculin units per test

sanofi